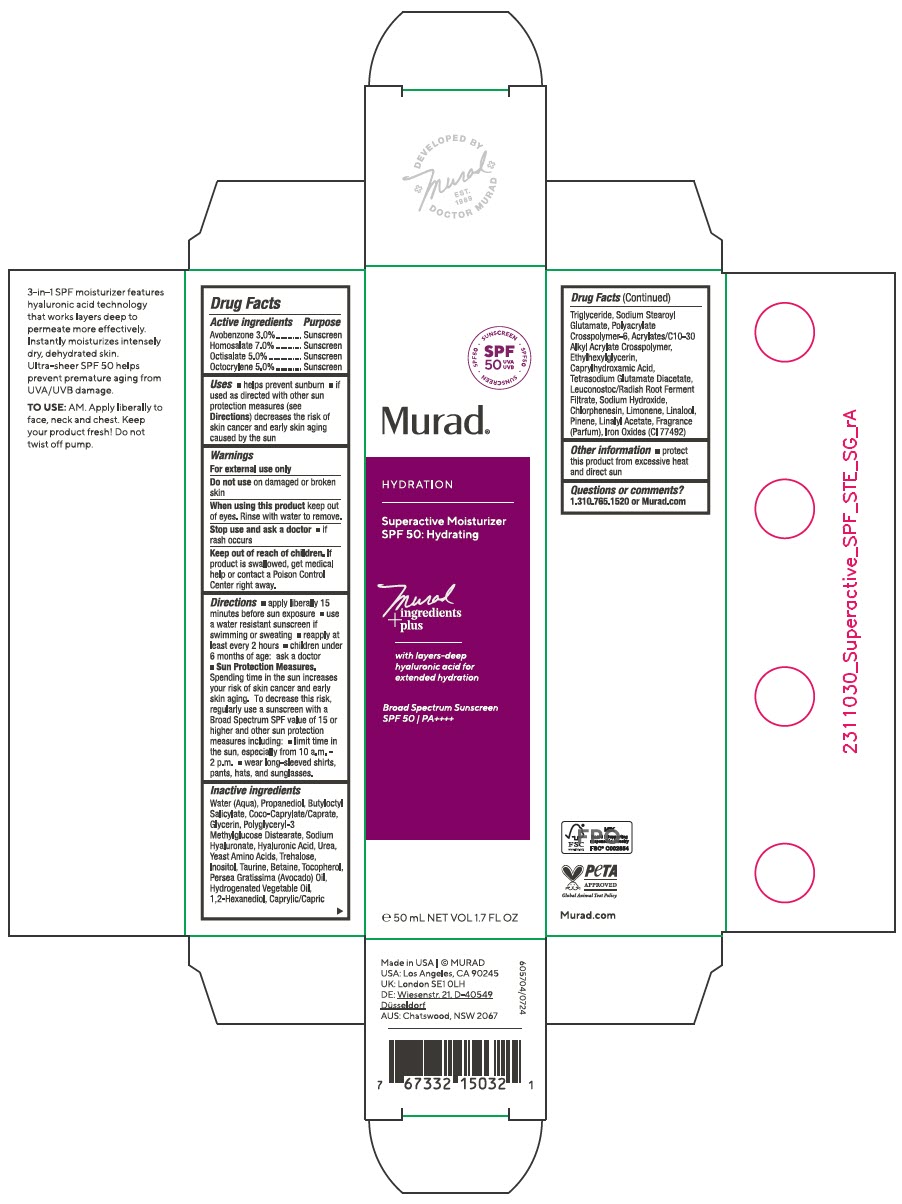 DRUG LABEL: Superactive Moisturizer SPF 50 Hydrating
NDC: 70381-132 | Form: CREAM
Manufacturer: Murad, LLC
Category: otc | Type: HUMAN OTC DRUG LABEL
Date: 20250326

ACTIVE INGREDIENTS: AVOBENZONE 3 g/100 mL; HOMOSALATE 7 g/100 mL; OCTISALATE 5 g/100 mL; OCTOCRYLENE 5 g/100 mL
INACTIVE INGREDIENTS: WATER; PROPANEDIOL; BUTYLOCTYL SALICYLATE; COCOYL CAPRYLOCAPRATE; GLYCERIN; POLYGLYCERYL-3 METHYLGLUCOSE DISTEARATE; HYALURONATE SODIUM; HYALURONIC ACID; UREA; AMINO ACIDS, SOURCE UNSPECIFIED; TREHALOSE; INOSITOL; TAURINE; BETAINE; TOCOPHEROL; AVOCADO OIL; HYDROGENATED AVOCADO OIL; 1,2-HEXANEDIOL; MEDIUM-CHAIN TRIGLYCERIDES; SODIUM STEAROYL GLUTAMATE; AMMONIUM ACRYLOYLDIMETHYLTAURATE, DIMETHYLACRYLAMIDE, LAURYL METHACRYLATE AND LAURETH-4 METHACRYLATE COPOLYMER, TRIMETHYLOLPROPANE TRIACRYLATE CROSSLINKED (45000 MPA.S); ACRYLATES/C10-30 ALKYL ACRYLATE CROSSPOLYMER (60000 MPA.S); ETHYLHEXYLGLYCERIN; CAPRYLHYDROXAMIC ACID; TETRASODIUM GLUTAMATE DIACETATE; LEUCONOSTOC/RADISH ROOT FERMENT FILTRATE; SODIUM HYDROXIDE; CHLORPHENESIN; LIMONENE, (+)-; LINALOOL, (+)-; PINENE; LINALYL ACETATE; FERRIC OXIDE YELLOW

Superactive Moisturizer SPF 50: Hydrating
SPF 50

Drug Facts

ACTIVE INGREDIENT

Active ingredients | Purpose
Avobenzone 3.0% | Sunscreen
Homosalate 7.0% | Sunscreen
Octisalate 5.0% | Sunscreen
Octocrylene 5.0% | Sunscreen

Uses

- helps prevent sunburn
- if used as directed with other sun protection measures (see Directions) decreases the risk of skin cancer and early skin aging caused by the sun

Warnings

For external use only

Do not use on damaged or broken skin

When using this product keep out of eyes. Rinse with water to remove.

Stop use and ask a doctor

- if rash occurs

Keep out of reach of children. If product is swallowed, get medical help or contact a Poison Control Center right away.

Directions

- apply liberally 15 minutes before sun exposure
- use a water resistant sunscreen if swimming or sweating
- reapply at least every 2 hours
- children under 6 months of age: ask a doctor
- Sun Protection Measures. Spending time in the sun increases your risk of skin cancer and early skin aging. To decrease this risk, regularly use a sunscreen with a Broad Spectrum SPF value of 15 or higher and other sun protection measures including:
  - limit time in the sun, especially from 10 a.m. - 2 p.m.
  - wear long-sleeved shirts, pants, hats, and sunglasses.

Inactive ingredients

Water (Aqua), Propanediol, Butyloctyl Salicylate, Coco-Caprylate/Caprate, Glycerin, Polyglyceryl-3 Methylglucose Distearate, Sodium Hyaluronate, Hyaluronic Acid, Urea, Yeast Amino Acids, Trehalose, Inositol, Taurine, Betaine, Tocopherol, Persea Gratissima (Avocado) Oil, Hydrogenated Vegetable Oil, 1,2-Hexanediol, Caprylic/Capric Triglyceride, Sodium Stearoyl Glutamate, Polyacrylate Crosspolymer-6, Acrylates/C10-30 Alkyl Acrylate Crosspolymer, Ethylhexylglycerin, Caprylhydroxamic Acid, Tetrasodium Glutamate Diacetate, Leuconostoc/Radish Root Ferment Filtrate, Sodium Hydroxide, Chlorphenesin, Limonene, Linalool, Pinene, Linalyl Acetate, Fragrance (Parfum), Iron Oxides (CI 77492)

Other information

- protect this product from excessive heat and direct sun

Questions or comments?

1.310.765.1520 or Murad.com

PRINCIPAL DISPLAY PANEL - 50 mL Bottle Carton

SPF
50
UVA
UVB

• SUNSCREEN • SPF50 • SUNSCREEN • SPF50

Murad®

HYDRATION

Superactive Moisturizer
SPF 50: Hydrating

Murad
ingredients
+ plus

with layers-deep
hyaluronic acid for
extended hydration

Broad Spectrum Sunscreen
SPF 50 / PA++++

℮ 50 mL NET VOL 1.7 FL OZ